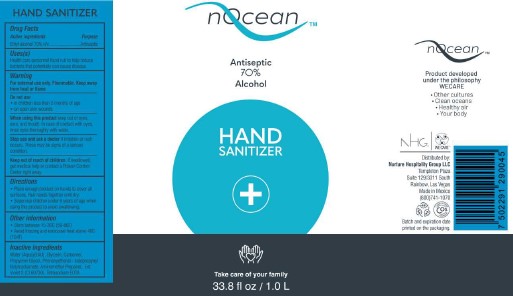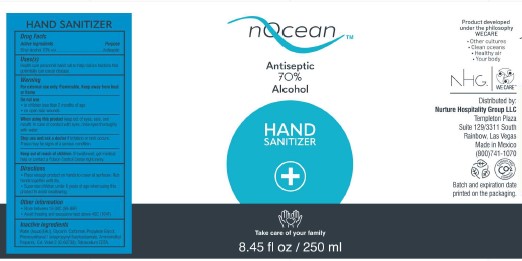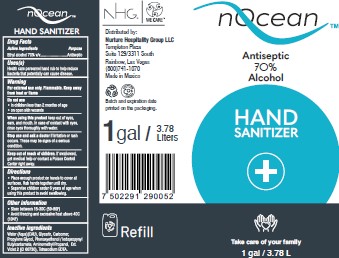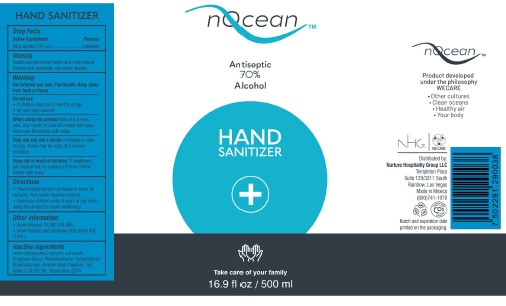 DRUG LABEL: Hand Sanitizer
NDC: 75470-410 | Form: GEL
Manufacturer: Tecnoglobal Ph7, S.a. De C.v.
Category: otc | Type: HUMAN OTC DRUG LABEL
Date: 20200825

ACTIVE INGREDIENTS: ALCOHOL 70 mL/100 mL
INACTIVE INGREDIENTS: GLYCERIN; WATER; AMINOMETHYLPROPANOL; EDETATE SODIUM; CARBOMER 940; PROPYLENE GLYCOL; PHENOXYETHANOL; IODOPROPYNYL BUTYLCARBAMATE; EXT. D&C VIOLET NO. 2

Noean 410-01 to 410-4

Active Ingredient(s)

Alcohol 70% v/v. Purpose: Antiseptic

Purpose

Antiseptic, Hand Sanitizer

Use

Hand Sanitizer to help reduce bacteria that potentially can cause disease.

Warnings

For external use only. Flammable. Keep away from heat or flame

Do not use

- in children less than 2 months of age
- on open skin wounds

When using this product keep out of eyes, ears, and mouth. In case of contact with eyes, rinse eyes thoroughly with water.

Stop use and ask a doctor if irritation or rash occurs. These may be signs of a serious condition.

Keep out of reach of children. If swallowed, get medical help or contact a Poison Control Center right away.

Directions

- Place enough product on hands to cover all surfaces. Rub hands together until dry.
- Supervise children under 6 years of age when using this product to avoid swallowing.

Other information

- Store between 15-30C (59-86F)
- Avoid freezing and excessive heat above 40C (104F)

Inactive ingredients

water, glycerin, carbomer, proplyene glycol, phenoxyethanol/iodopropynylbutylcarbamate, aminomethlypropanol, ext. violet 2, tetrasodium EDTA.

Package Label - Principal Display Panel

250 mL NDC: 75470-410-04

250 mL NDC: 75470-410-03

250 mL NDC: 75470-410-02

250 mL NDC: 75470-410-01